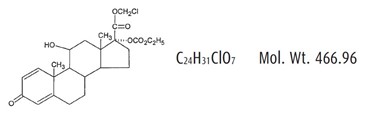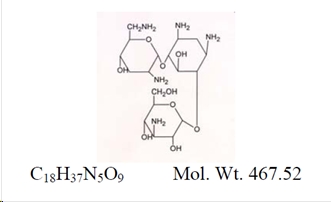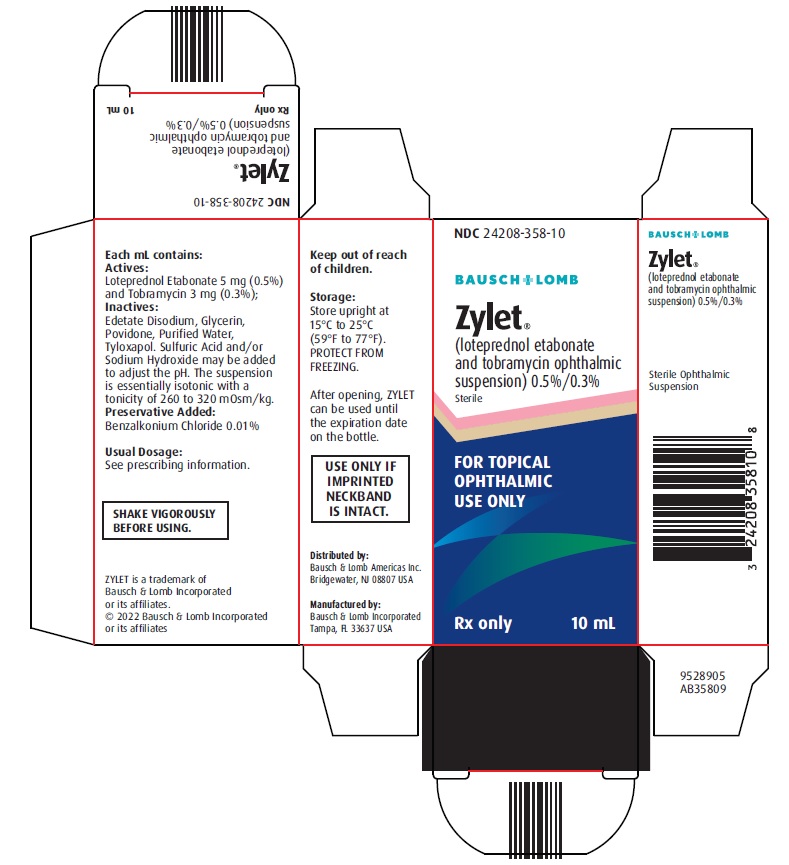 DRUG LABEL: Zylet
NDC: 24208-358 | Form: SUSPENSION/ DROPS
Manufacturer: Bausch & Lomb Incorporated
Category: prescription | Type: HUMAN PRESCRIPTION DRUG LABEL
Date: 20220430

ACTIVE INGREDIENTS: LOTEPREDNOL ETABONATE 5 mg/1 mL; TOBRAMYCIN 3 mg/1 mL
INACTIVE INGREDIENTS: GLYCERIN; POVIDONE, UNSPECIFIED; WATER; TYLOXAPOL; BENZALKONIUM CHLORIDE; SULFURIC ACID; SODIUM HYDROXIDE; EDETATE DISODIUM

HIGHLIGHTS OF PRESCRIBING INFORMATION

These highlights do not include all the information needed to use ZYLET safely and effectively. See full prescribing information for ZYLET.
ZYLET® (loteprednol etabonate and tobramycin ophthalmic
suspension) 0.5%/0.3%, for topical ophthalmic use
Initial U.S. Approval: 2004

1 INDICATIONS AND USAGE

ZYLET is a combination of loteprednol etabonate, a corticosteroid, and tobramycin, an aminoglycoside antibacterial, indicated for steroid-responsive inflammatory ocular conditions for which a corticosteroid is indicated and where superficial bacterial ocular infection or a risk of bacterial ocular infection exists. (1)

2 DOSAGE AND ADMINISTRATION

Apply one or two drops of ZYLET into the conjunctival sac of the affected eye every four to six hours. (2.1)

3 DOSAGE FORMS AND STRENGTHS

Ophthalmic suspension containing 5 mg/mL (0.5%) loteprednol etabonate and 3 mg/mL (0.3%) tobramycin. (3)

4 CONTRAINDICATIONS

ZYLET, as with other steroid anti-infective ophthalmic combination drugs, is contraindicated in most viral diseases of the cornea and conjunctiva including epithelial herpes simplex keratitis (dendritic keratitis), vaccinia, and varicella, and also in mycobacterial infection of the eye and fungal diseases of ocular structures. (4.1)

5 WARNINGS AND PRECAUTIONS

- Intraocular Pressure (IOP) Increase: Prolonged use of corticosteroids may result in glaucoma with damage to the optic nerve, defects in visual acuity and fields of vision. If this product is used for 10 days or longer, IOP should be monitored. (5.1)
- Cataracts: Use of corticosteroids may result in posterior subcapsular cataract formation. (5.2)
- Delayed Healing: The use of steroids after cataract surgery may delay healing and increase the incidence of bleb formation. In those diseases causing thinning of the cornea or sclera, perforations have been known to occur with the use of topical steroids. The initial prescription and renewal of the medication order should be made by a physician only after examination of the patient with the aid of a magnification such as slit lamp biomicroscopy and, where appropriate, fluorescein staining. (5.3)
- Bacterial Infections: Prolonged use of corticosteroids may suppress the host response and thus increase the hazard of secondary ocular infection. In acute purulent conditions, steroids may mask infection or enhance existing infection. If signs and symptoms fail to improve after 2 days, the patient should be re-evaluated. (5.4)
- Viral Infections: Employment of a corticosteroid medication in the treatment of patients with a history of herpes simplex requires great caution. Use of ocular steroids may prolong the course and may exacerbate the severity of many viral infections of the eye (including herpes simplex). (5.5)
- Fungal Infections: Fungal infections of the cornea are particularly prone to develop coincidentally with long-term local steroid application. Fungus invasion must be considered in any persistent corneal ulceration where a steroid has been used or is in use. (5.6)

6 ADVERSE REACTIONS

Most common adverse reactions reported in patients were injection and superficial punctate keratitis, increased intraocular pressure, burning and stinging upon instillation. (6)

To report SUSPECTED ADVERSE REACTIONS, contact Bausch & Lomb Incorporated at 1-800-553-5340 or FDA at 1-800-FDA-1088 or www.fda.gov/medwatch.

FULL PRESCRIBING INFORMATION

1 INDICATIONS AND USAGE

ZYLET® (loteprednol etabonate and tobramycin ophthalmic suspension), 0.5%/0.3% is a topical anti-infective and corticosteroid combination for steroid-responsive inflammatory ocular conditions for which a corticosteroid is indicated and where superficial bacterial ocular infection or a risk of bacterial ocular infection exists.

Ocular steroids are indicated in inflammatory conditions of the palpebral and bulbar conjunctiva, cornea and anterior segment of the globe such as allergic conjunctivitis, acne rosacea, superficial punctate keratitis, herpes zoster keratitis, iritis, cyclitis, and where the inherent risk of steroid use in certain infective conjunctivitides is accepted to obtain a diminution in edema and inflammation. They are also indicated in chronic anterior uveitis and corneal injury from chemical, radiation or thermal burns, or penetration of foreign bodies.

The use of a combination drug with an anti-infective component is indicated where the risk of superficial ocular infection is high or where there is an expectation that potentially dangerous numbers of bacteria will be present in the eye.

The particular anti-infective drug in this product (tobramycin) is active against the following common bacterial eye pathogens:

Staphylococci, including S. aureus and S. epidermidis (coagulase-positive and coagulase-negative), including penicillin-resistant strains. Streptococci, including some of the Group A-beta-hemolytic species, some nonhemolytic species, and some Streptococcus pneumoniae, Pseudomonas aeruginosa, Escherichia coli, Klebsiella pneumoniae, Enterobacter aerogenes, Proteus mirabilis, Morganella morganii, most Proteus vulgaris strains, Haemophilus influenzae, and H. aegyptius, Moraxella lacunata, Acinetobacter calcoaceticus and some Neisseria species.

2 DOSAGE AND ADMINISTRATION

2.1 Recommended Dosing

Apply one or two drops of ZYLET into the conjunctival sac of the affected eye every four to six hours. During the initial 24 to 48 hours, the dosing may be increased, to every one to two hours. Frequency should be decreased gradually as warranted by improvement in clinical signs. Care should be taken not to discontinue therapy prematurely.

2.2 Prescription Guideline

Not more than 20 mL should be prescribed initially and the prescription should not be refilled without further evaluation [see Warnings and Precautions (5.3)].

3 DOSAGE FORMS AND STRENGTHS

Ophthalmic suspension containing 5 mg/mL (0.5%) loteprednol etabonate and 3 mg/mL (0.3%) tobramycin.

4 CONTRAINDICATIONS

4.1 Nonbacterial Etiology

ZYLET, as with other steroid anti-infective ophthalmic combination drugs, is contraindicated in most viral diseases of the cornea and conjunctiva including epithelial herpes simplex keratitis (dendritic keratitis), vaccinia, and varicella, and also in mycobacterial infection of the eye and fungal diseases of ocular structures.

5 WARNINGS AND PRECAUTIONS

5.1 Intraocular Pressure (IOP) Increase

Prolonged use of corticosteroids may result in glaucoma with damage to the optic nerve, defects in visual acuity and fields of vision. Steroids should be used with caution in the presence of glaucoma.

If this product is used for 10 days or longer, intraocular pressure should be monitored.

5.2 Cataracts

Use of corticosteroids may result in posterior subcapsular cataract formation.

5.3 Delayed Healing

The use of steroids after cataract surgery may delay healing and increase the incidence of bleb formation. In those diseases causing thinning of the cornea or sclera, perforations have been known to occur with the use of topical steroids. The initial prescription and renewal of the medication order should be made by a physician only after examination of the patient with the aid of magnification such as a slit lamp biomicroscopy and, where appropriate, fluorescein staining.

5.4 Bacterial Infections

Prolonged use of corticosteroids may suppress the host response and thus increase the hazard of secondary ocular infections. In acute purulent conditions of the eye, steroids may mask infection or enhance existing infection. If signs and symptoms fail to improve after 2 days, the patient should be re-evaluated.

5.5 Viral Infections

Employment of a corticosteroid medication in the treatment of patients with a history of herpes simplex requires great caution. Use of ocular steroids may prolong the course and may exacerbate the severity of many viral infections of the eye (including herpes simplex).

5.6 Fungal Infections

Fungal infections of the cornea are particularly prone to develop coincidentally with long-term local steroid application. Fungus invasion must be considered in any persistent corneal ulceration where a steroid has been used or is in use. Fungal cultures should be taken when appropriate.

5.7 Aminoglycoside Hypersensitivity

Sensitivity to topically applied aminoglycosides may occur in some patients. If hypersensitivity develops with this product, discontinue use and institute appropriate therapy.

5.8 Risk of Contamination

Do not allow the dropper tip to touch any surface, as this may contaminate the suspension.

5.9 Contact Lens Wear

As with all ophthalmic preparations containing benzalkonium chloride, patients should be advised not to wear soft contact lenses when using ZYLET.

6 ADVERSE REACTIONS

Adverse reactions have occurred with steroid/anti-infective combination drugs which can be attributed to the steroid component, the anti-infective component, or the combination.

ZYLET

In a 42-day safety study comparing ZYLET to placebo, ocular adverse reactions included injection (approximately 20%) and superficial punctate keratitis (approximately 15%). Increased intraocular pressure was reported in 10% (ZYLET) and 4% (placebo) of subjects. Nine percent (9%) of ZYLET subjects reported burning and stinging upon instillation.

Ocular reactions reported with an incidence less than 4% include vision disorders, discharge, itching, lacrimation disorder, photophobia, corneal deposits, ocular discomfort, eyelid disorder, and other unspecified eye disorders.

The incidence of non-ocular reactions reported in approximately 14% of subjects was headache; all other non-ocular reactions had an incidence of less than 5%.

Loteprednol etabonate ophthalmic suspension 0.2% - 0.5%

Reactions associated with ophthalmic steroids include elevated intraocular pressure, which may be associated with infrequent optic nerve damage, visual acuity and field defects, posterior subcapsular cataract formation, delayed wound healing and secondary ocular infection from pathogens including herpes simplex, and perforation of the globe where there is thinning of the cornea or sclera.

In a summation of controlled, randomized studies of individuals treated for 28 days or longer with loteprednol etabonate, the incidence of significant elevation of intraocular pressure (≥10 mm Hg) was 2% (15/901) among patients receiving loteprednol etabonate, 7% (11/164) among patients receiving 1% prednisolone acetate and 0.5% (3/583) among patients receiving placebo.

Tobramycin ophthalmic solution 0.3%

The most frequent adverse reactions to topical tobramycin are hypersensitivity and localized ocular toxicity, including lid itching and swelling and conjunctival erythema. These reactions occur in less than 4% of patients. Similar reactions may occur with the topical use of other aminoglycoside antibiotics.

Secondary Infection

The development of secondary infection has occurred after use of combinations containing steroids and antimicrobials. Fungal infections of the cornea are particularly prone to develop coincidentally with long-term applications of steroids.

The possibility of fungal invasion must be considered in any persistent corneal ulceration where steroid treatment has been used.

Secondary bacterial ocular infection following suppression of host responses also occurs.

8 USE IN SPECIFIC POPULATIONS

8.1 Pregnancy

Risk Summary

There are no adequate and well-controlled studies with loteprednol etabonate or tobramycin in pregnant women.

Loteprednol etabonate produced teratogenicity at clinically relevant doses in the rabbit and rat when administered orally during pregnancy. Loteprednol etabonate produced malformations when administered orally to pregnant rabbits at doses ≥ 0.54 times the recommended human ophthalmic dose (RHOD) and to pregnant rats at doses ≥ 13 times the RHOD. In pregnant rats receiving oral doses of loteprednol etabonate during the period equivalent to the last trimester of pregnancy through lactation in humans, survival of offspring was reduced at doses ≥ 1.3 times the RHOD. Maternal toxicity was observed in rats at doses ≥ 135 times the RHOD, and a maternal no observed adverse effect level (NOAEL) was established at 13 times the RHOD.

Abortions were observed in pregnant rabbits administered tobramycin via subcutaneous injection at 180 times the RHOD. Tobramycin did not affect fetal development when administered by subcutaneous injection to pregnant rats at doses 450 times the RHOD.

The background risk of major birth defects and miscarriage for the indicated population is unknown. However, the background risk in the U.S. general population of major birth defects is 2 to 4%, and of miscarriage is 15 to 20%, of clinically recognized pregnancies.

Data

Animal Data

Embryofetal studies were conducted in pregnant rabbits administered loteprednol etabonate by oral gavage on gestation days 6 to 18, to target the period of organogenesis. Loteprednol etabonate produced fetal malformations at doses ≥ 0.1 mg/kg/day (0.54 times the recommended human ophthalmic dose (RHOD) based on body surface area, assuming 100% absorption of loteprednol etabonate). Spina bifida (including meningocele) was observed at doses ≥ 0.1 mg/kg/day, and exencephaly and craniofacial malformations were observed at doses ≥ 0.4 mg/kg/day (2.1 times the RHOD). At 3 mg/kg/day (16 times the RHOD), loteprednol etabonate was associated with increased incidences of abnormal left common carotid artery, limb flexures, umbilical hernia, scoliosis, and delayed ossification. Abortion and embryofetal lethality (resorption) occurred at doses ≥ 6 mg/kg/day (32 times the RHOD). A NOAEL for developmental toxicity was not established in this study. The NOAEL for maternal toxicity in rabbits was 3 mg/kg/day.

Embryofetal studies were conducted in pregnant rats administered loteprednol etabonate by oral gavage on gestation days 6 to 15, to target the period of organogenesis. Loteprednol etabonate produced fetal malformations, including absent innominate artery at doses ≥ 5 mg/kg/day (13 times the RHOD); and cleft palate, agnathia, cardiovascular defects, umbilical hernia, decreased fetal body weight and decreased skeletal ossification at doses ≥ 50 mg/kg/day (135 times the RHOD). Embryofetal lethality (resorption) was observed at 100 mg/kg/day (270 times the RHOD). The NOAEL for developmental toxicity in rats was 0.5 mg/kg/day (1.3 times the RHOD). Loteprednol etabonate was maternally toxic (reduced body weight gain) at doses of ≥ 50 mg/kg/day. The NOAEL for maternal toxicity was 5 mg/kg/day.

A peri-/postnatal study was conducted in rats administered loteprednol etabonate by oral gavage from gestation day 15 (start of fetal period) to postnatal day 21 (the end of lactation period). At doses ≥ 0.5 mg/kg/day (1.3 times the RHOD), reduced survival was observed in live-born offspring. Doses ≥ 5 mg/kg/day (13 times the RHOD) caused umbilical hernia/incomplete gastrointestinal tract. Doses ≥ 50 mg/kg/day (135 times the RHOD) produced maternal toxicity (reduced body weight gain, death), decreased number of live-born offspring, decreased birth weight, and delays in postnatal development. A developmental NOAEL was not established in this study. The NOAEL for maternal toxicity was 5 mg/kg/day.

An embryofetal study was conducted in pregnant rabbits administered 20 or 40 mg/kg/day tobramycin by subcutaneous injection on gestational days 6 to 18, to target the period of organogenesis. Abortions and maternal toxicity (renal nephrosis and cortical tubular necrosis) were observed at both dose levels. The developmental and maternal lowest observed adverse effect level (LOAEL) is 20 mg/kg/day (180 times the RHOD based on body surface area, assuming 100% absorption of tobramycin). An embryofetal study was conducted in pregnant rats administered 50 or 100 mg/kg/day tobramycin by subcutaneous injection on gestational days 6 to 15, to target the period of organogenesis. No effects on development, reproduction, or maternal toxicity were reported. The developmental and maternal NOAEL is 100 mg/kg/day (450 times the RHOD).

8.2 Lactation

There are no data on the presence of loteprednol etabonate or tobramycin in human milk, the effects on the breastfed infant, or the effects on milk production. The developmental and health benefits of breastfeeding should be considered, along with the mother’s clinical need for ZYLET and any potential adverse effects on the breastfed infant from ZYLET.

8.4 Pediatric Use

Two trials were conducted to evaluate the safety and efficacy of ZYLET (loteprednol etabonate and tobramycin ophthalmic suspension) in pediatric subjects age zero to six years; one was in subjects with lid inflammation and the other was in subjects with blepharoconjunctivitis.

In the lid inflammation trial, ZYLET with warm compresses did not demonstrate efficacy compared to vehicle with warm compresses. Patients received warm compress lid treatment plus ZYLET or vehicle for 14 days. The majority of patients in both treatment groups showed reduced lid inflammation.

In the blepharoconjunctivitis trial, ZYLET did not demonstrate efficacy compared to vehicle, loteprednol etabonate ophthalmic suspension, or tobramycin ophthalmic solution. There was no difference between treatment groups in mean change from baseline blepharoconjunctivitis score at Day 15.

There were no differences in safety assessments between the treatment groups in either trial.

8.5 Geriatric Use

No overall differences in safety and effectiveness have been observed between elderly and younger patients.

11 DESCRIPTION

ZYLET (loteprednol etabonate and tobramycin ophthalmic suspension) is a sterile, multiple dose topical anti-inflammatory corticosteroid and anti-infective combination for ophthalmic use. Both loteprednol etabonate and tobramycin are white to off-white powders. The chemical structures of loteprednol etabonate and tobramycin are shown below.

Loteprednol etabonate:

Chemical name: chloromethyl 17α-[(ethoxycarbonyl)oxy]-11β-hydroxy-3-oxoandrosta-1,4-diene-17β-carboxylate

Tobramycin:

Chemical name:

O-3-Amino-3-deoxy-α-D-glucopyranosyl-(1→4)-O-[2,6-diamino-2,3,6-trideoxy-α-D-ribo-hexopyranosyl-(1→6)]-2-deoxystreptamine

Each mL contains: Actives: Loteprednol Etabonate 5 mg (0.5%) and Tobramycin 3 mg (0.3%). Inactives: Edetate Disodium, Glycerin, Povidone, Purified Water, Tyloxapol, and Benzalkonium Chloride 0.01% (preservative). Sulfuric Acid and/or Sodium Hydroxide may be added to adjust the pH to 5.5 to 6.2. The suspension is essentially isotonic with a tonicity of 260 to 320 mOsm/kg.

12 CLINICAL PHARMACOLOGY

12.1 Mechanism of Action

Corticosteroids inhibit the inflammatory response to a variety of inciting agents and probably delay or slow healing. They inhibit the edema, fibrin deposition, capillary dilation, leukocyte migration, capillary proliferation, fibroblast proliferation, deposition of collagen, and scar formation associated with inflammation. There is no generally accepted explanation for the mechanism of action of ocular corticosteroids. However, corticosteroids are thought to act by the induction of phospholipase A2 inhibitory proteins, collectively called lipocortins. It is postulated that these proteins control the biosynthesis of potent mediators of inflammation such as prostaglandins and leukotrienes by inhibiting the release of their common precursor arachidonic acid.

Arachidonic acid is released from membrane phospholipids by phospholipase A2. Corticosteroids are capable of producing a rise in intraocular pressure.

Loteprednol etabonate is structurally similar to other corticosteroids. However, the number 20 position ketone group is absent.

The anti-infective component in the combination (tobramycin) is included to provide action against susceptible organisms. In vitro studies have demonstrated that tobramycin is active against susceptible strains of the following microorganisms:

Staphylococci, including S. aureus and S. epidermidis (coagulase-positive and coagulase-negative), including penicillin-resistant strains.

Streptococci, including some of the Group A-beta-hemolytic species, some nonhemolytic species, and some Streptococcus pneumoniae. Pseudomonas aeruginosa, Escherichia coli, Klebsiella pneumoniae, Enterobacter aerogenes, Proteus mirabilis, Morganella morganii, most Proteus vulgaris strains, Haemophilus influenzae and H. aegyptius, Moraxella lacunata, Acinetobacter calcoaceticus and some Neisseria species.

12.3 Pharmacokinetics

In a controlled clinical study of ocular penetration, the levels of loteprednol etabonate in the aqueous humor were found to be comparable between LOTEMAX® and ZYLET treatment groups.

Results from a bioavailability study in normal volunteers established that plasma levels of loteprednol etabonate and Δ^1 cortienic acid etabonate (PJ 91), its primary, inactive metabolite, were below the limit of quantitation (1 ng/mL) at all sampling times.

The results were obtained following the ocular administration of one drop in each eye of 0.5% loteprednol etabonate ophthalmic suspension 8 times daily for 2 days or 4 times daily for 42 days. This study suggests that limited (<1 ng/mL) systemic absorption occurs with 0.5% loteprednol etabonate.

13 NONCLINICAL TOXICOLOGY

13.1 Carcinogenesis, Mutagenesis, Impairment of Fertility

Carcinogenesis

Long-term animal studies have not been conducted to evaluate the carcinogenic potential of loteprednol etabonate or tobramycin.

Mutagenesis

Loteprednol etabonate was not genotoxic in vitro in the Ames test, the mouse lymphoma TK assay, a chromosome aberration test in human lymphocytes, or in an in vivo mouse micronucleus assay.

Impairment of Fertility

Oral treatment of female and male rats with 25 mg/kg/day of loteprednol etabonate (67 times the RHOD based on body surface area, assuming 100% absorption) prior to and during mating caused preimplantation loss and decreased the number of live fetuses/live births. The NOAEL for fertility in rats was 5 mg/kg/day (13 times the RHOD). Subcutaneous administration of male and female rats with tobramycin did not affect mating behavior or cause impairment of fertility at 100 mg/kg/day (450 times the RHOD based on body surface area, assuming 100% absorption).

16 HOW SUPPLIED/STORAGE AND HANDLING

ZYLET (loteprednol etabonate and tobramycin ophthalmic suspension) 0.5%/0.3% is supplied in a white low density polyethylene plastic bottle with a white controlled drop tip and a white polypropylene cap in the following sizes:

NDC 24208-358-05 5 mL fill in a 7.5 mL bottle

NDC 24208-358-10 10 mL fill in a 10 mL bottle

USE ONLY IF IMPRINTED NECKBAND IS INTACT.

Storage: Store upright at 15ºC to 25ºC (59ºF to 77ºF). PROTECT FROM FREEZING. SHAKE VIGOROUSLY BEFORE USING. After opening, ZYLET can be used until the expiration date on the bottle.

17 PATIENT COUNSELING INFORMATION

Risk of Contamination

This product is sterile when packaged. Advise patients not to allow the dropper tip to touch any surface, as this may contaminate the suspension.

Risk of Secondary Infection

Advise patients to consult a physician if pain develops, redness, itching or inflammation becomes aggravated.

Contact Lens Wear

As with all ophthalmic preparations containing benzalkonium chloride, advise patients not to wear soft contact lenses when using ZYLET.

Distributed by:
Bausch & Lomb Americas Inc.
Bridgewater, NJ 08807 USA
Manufactured by:
Bausch & Lomb Incorporated
Tampa, FL 33637 USA
ZYLET and LOTEMAX are trademarks of Bausch & Lomb Incorporated or its affiliates.

© 2022 Bausch & Lomb Incorporated or its affiliates

9007709 (FOLDED)
9004409 (FLAT)

PACKAGE/LABEL PRINCIPAL DISPLAY PANEL

NDC 24208-358-10
BAUSCH + LOMB
Zylet®
(loteprednol etabonate
and tobramycin ophthalmic
suspension) 0.5%/0.3%
Sterile

FOR TOPICAL
OPHTHALMIC
USE ONLY
Rx only

10 mL

9528905
AB35809